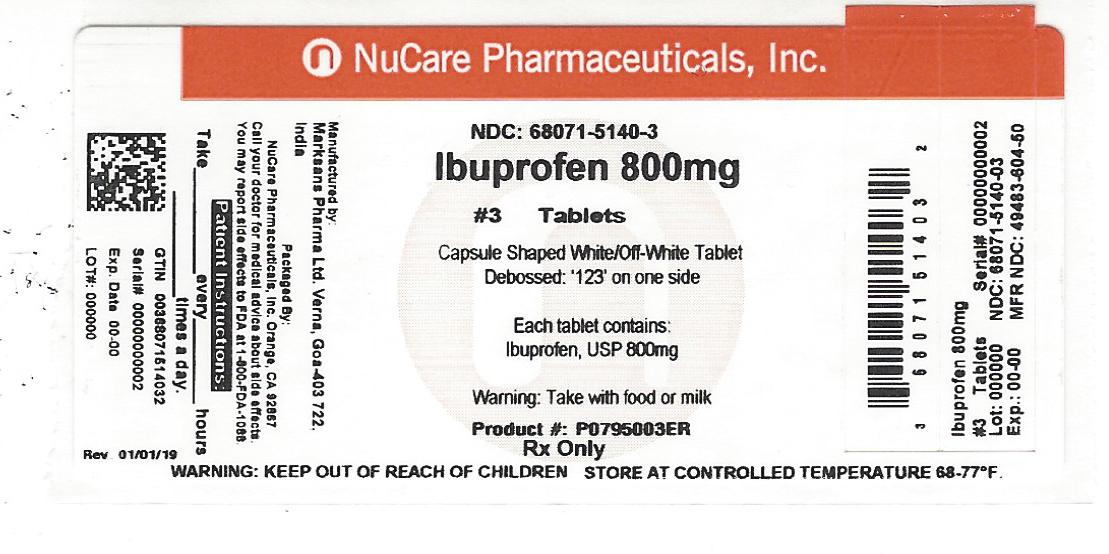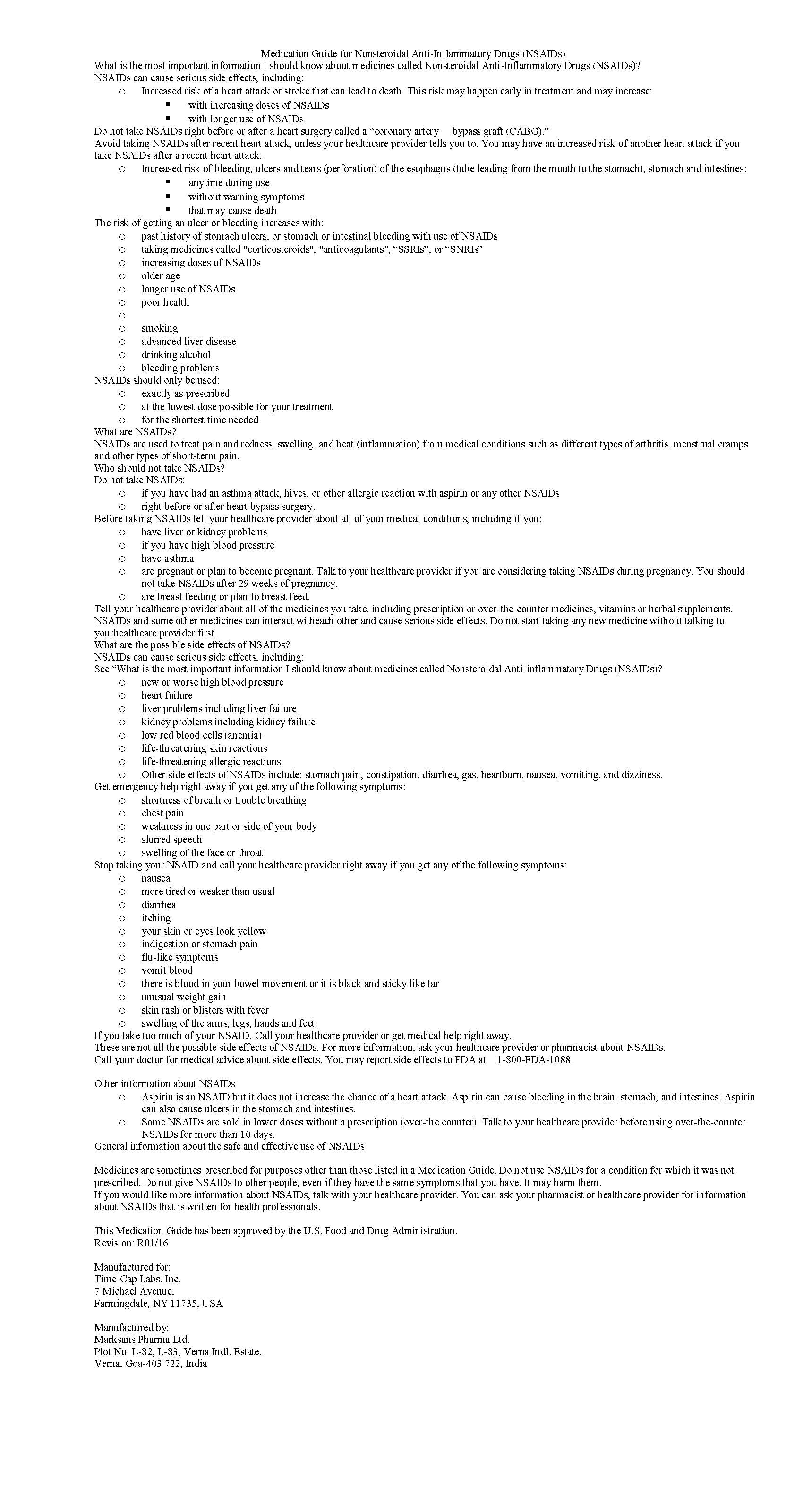 DRUG LABEL: IBUPROFEN
NDC: 68071-5140 | Form: TABLET, FILM COATED
Manufacturer: NuCare Pharmaceuticals,Inc.
Category: prescription | Type: HUMAN PRESCRIPTION DRUG LABEL
Date: 20250102

ACTIVE INGREDIENTS: IBUPROFEN 800 mg/1 1
INACTIVE INGREDIENTS: SILICON DIOXIDE; CROSCARMELLOSE SODIUM; MAGNESIUM STEARATE; CELLULOSE, MICROCRYSTALLINE; POLYETHYLENE GLYCOL, UNSPECIFIED; POLYVINYL ALCOHOL; STARCH, PREGELATINIZED CORN; TALC; TITANIUM DIOXIDE

IBUPROFEN 400 MG - 600 MG AND 800 MG TABLETS

HOW SUPPLIED

800 mg (white to off-white, capsule shaped, biconvex, film-coated tablets debossed with 123 on one side and plain on other side)

NDC 68071-5140-3 BOTTLES OF 3

NDC 68071-5140-6 BOTTLES OF 6